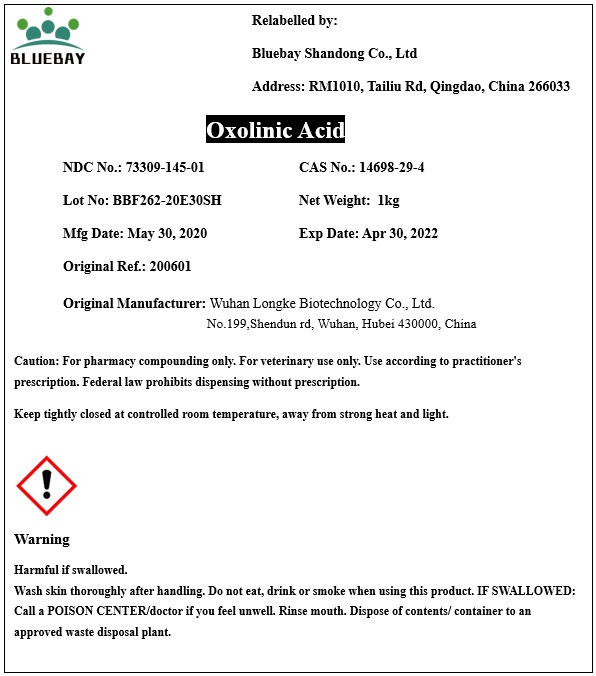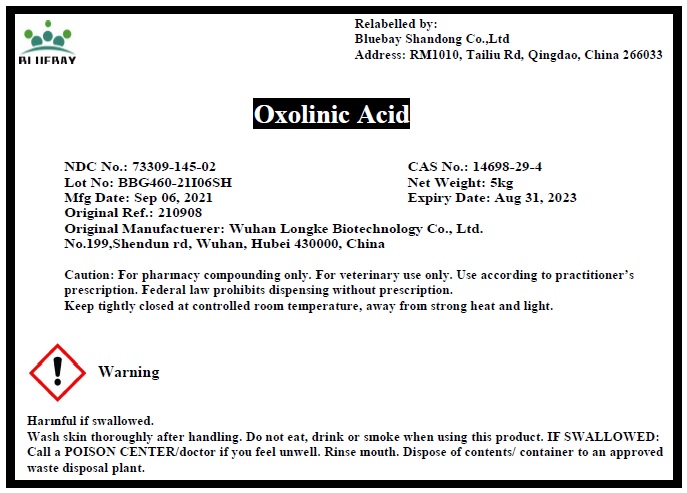 DRUG LABEL: Oxolinic Acid
NDC: 73309-145 | Form: POWDER
Manufacturer: BLUEBAY SHANDONG CO.,LTD
Category: other | Type: BULK INGREDIENT
Date: 20210924

ACTIVE INGREDIENTS: OXOLINIC ACID 1 kg/1 kg

Oxolinic Acid